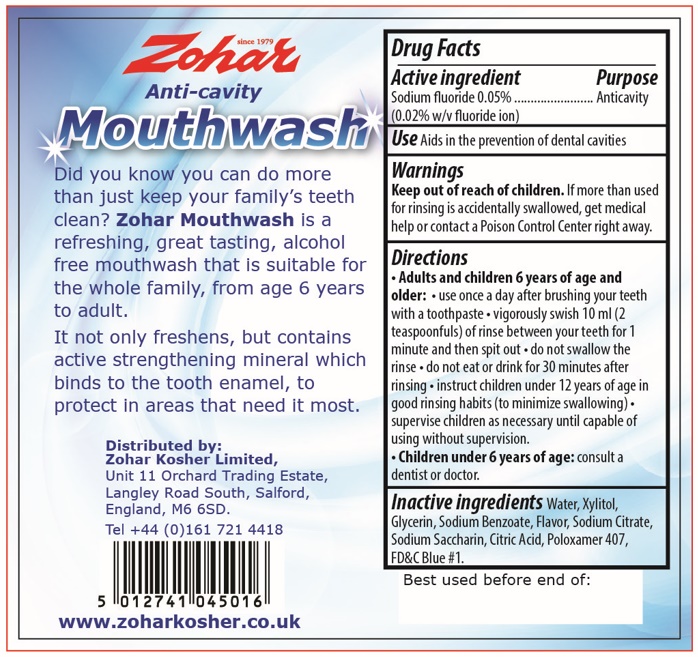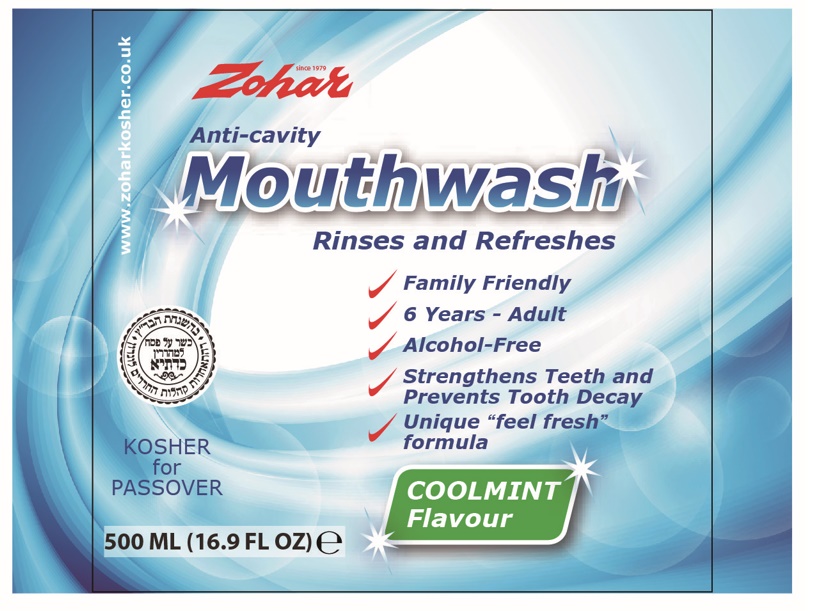 DRUG LABEL: Zohar Anti Cavity Mouthwash Coolmint Flavour
NDC: 84045-001 | Form: LIQUID
Manufacturer: ZOHAR KOSHER LIMITED
Category: otc | Type: HUMAN OTC DRUG LABEL
Date: 20240227

ACTIVE INGREDIENTS: SODIUM FLUORIDE 0.2 mg/1 mL
INACTIVE INGREDIENTS: WATER; XYLITOL; GLYCERIN; SODIUM BENZOATE; SODIUM CITRATE; SACCHARIN SODIUM; CITRIC ACID MONOHYDRATE; POLOXAMER 407; FD&C BLUE NO. 1

Zohar Anti-Cavity Mouthwash Coolmint Flavour

Active ingredient

Sodium fluoride 0.05% (0.02% w/v fluoride ion)

Purpose

Anticavity

Use

Aids in the prevention of dental cavities

Warnings

Keep out of reach of children.

If more than used for rinsing is accidentally swallowed, get medical help or contact a Poison Control Center right away.

Directions

- Adults and children 6 years of age and older:
- use once a day after brushing your teeth with a toothpaste
- vigorously swish 10 ml (2teaspoonfuls) of rinse between your teeth for 1 minute and then spit out
- do not swallow the rinse
- do not eat or drink for 30 minutes after rinsing
- instruct children under 12 years of age in good rinsing habits (to minimize swallowing)
- supervise children as necessary untill capable of using without supervision.
- Children under 6 years of age:consult a dentist or doctor.

Inactive ingredients

Water, Xylitol, Glycerin, Sodium Benzoate, Flavor, Sodium Citrate, Sodium Saccharin, Citric Acid, Poloxamer 407, FD&C Blue #1.